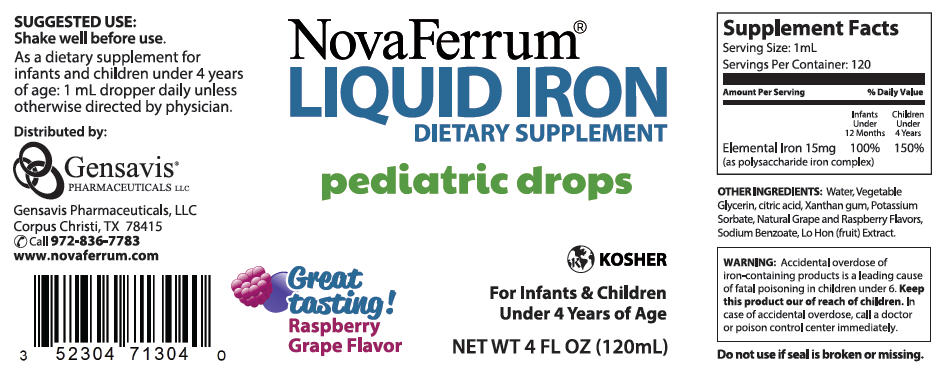 DRUG LABEL: NovaFerrum 
NDC: 52304-713 | Form: LIQUID
Manufacturer: Gensavis Pharmaceuticals, LLC
Category: other | Type: DIETARY SUPPLEMENT
Date: 20140124

ACTIVE INGREDIENTS: iron 15 mg/1 mL
INACTIVE INGREDIENTS: water; Citric Acid Monohydrate; Xanthan Gum; Potassium Sorbate; Sodium Benzoate; SIRAITIA GROSVENORII FRUIT

NovaFerrum
Liquid Iron Dietary Supplement
Pediatric Drops

Supplement Facts

Serving Size: 1mL

Servings Per Container: 120

Amount Per Serving | % Daily Value
 | Infants under 12 months | Children under 4 years
Elemental Iron 15mg | 100% | 150%
(as polysaccharide iron complex)

HEALTH CLAIM

OTHER INGREDIENTS: Water, Vegetable Glycerin, citric acid, Xanthan gum, Potassium Sorbate, Natural Grape and Raspberry Flavors, Sodium Benzoate, Lo Hon (fruit) Extract.

WARNING

Accidental overdose of iron-containing products is a leading cause of fatal poisoning in children under 6. Keep this product our of reach of children. In case of accidental overdose, call a doctor or poison control center immediately.

Do not use if seal is broken or missing.

Suggested use

Shake well before use.

As a dietary supplement for infants and children under 4 years of age: 1 mL dropper daily unless otherwise directed by physician.

WARNING

If you are pregnant or lactating, consult your physician before using this product.

Distributed by:
Gensavis Pharmaceuticals, LLC
Corpus Christi, TX 78415
Call 972-836-7783
www.novaferrum.com

PRINCIPAL DISPLAY PANEL - 120mL Bottle Label

NovaFerrum
Liquid Iron Dietary Supplement
Pediatric Drops

KOSHER
For Infants & Children Under 4 Years of Age
NET WT 4 FL OZ (120mL)

Great tasting!
Raspberry Grape Flavor